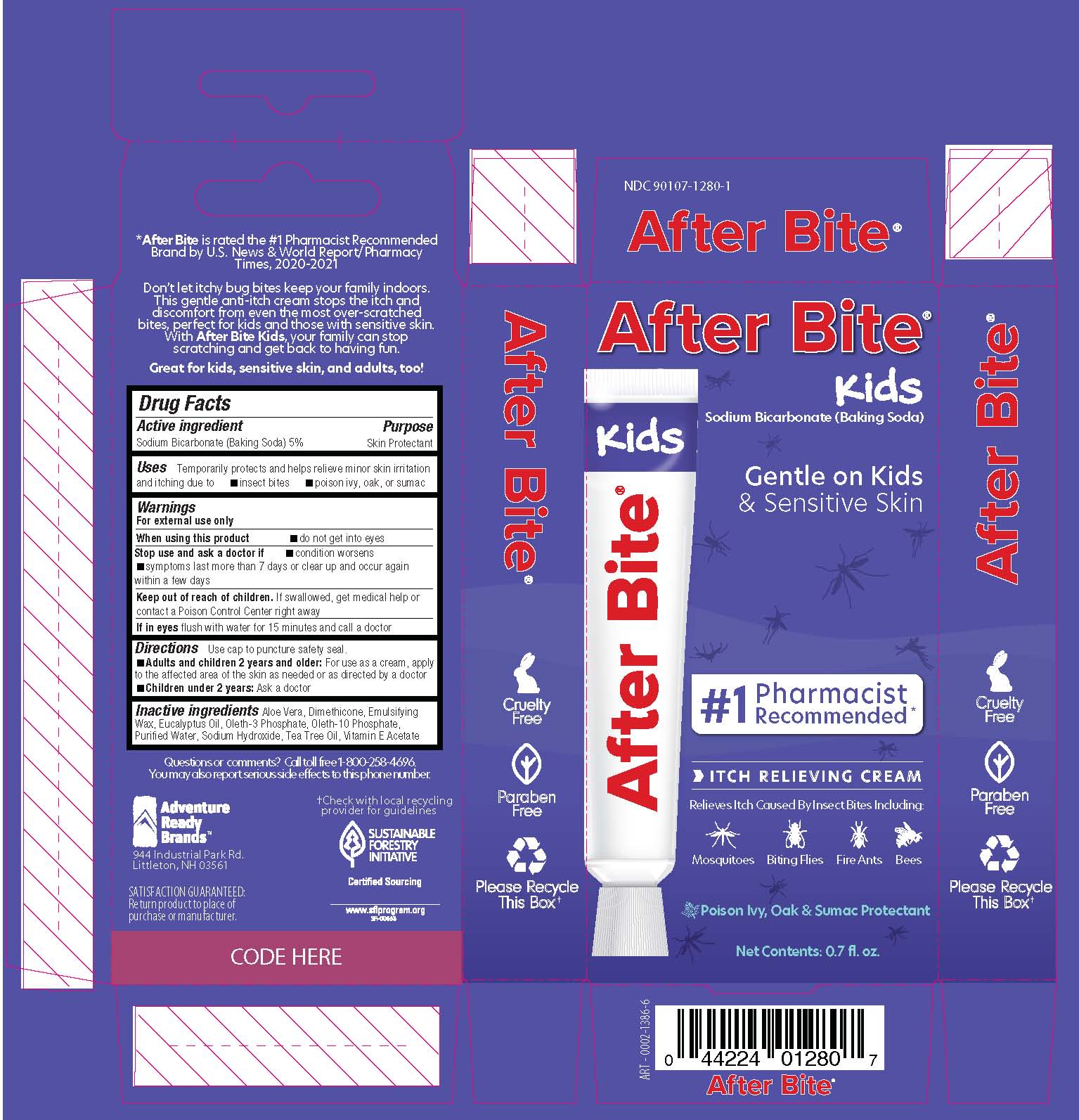 DRUG LABEL: After Bite Kids
NDC: 90107-1280 | Form: CREAM
Manufacturer: Adventure Ready Brands
Category: otc | Type: HUMAN OTC DRUG LABEL
Date: 20240216

ACTIVE INGREDIENTS: SODIUM BICARBONATE 1 g/20 g
INACTIVE INGREDIENTS: ALOE VERA LEAF 1.1 g/20 g; DIMETHICONE 0.1 g/20 g; EUCALYPTUS OIL 0.26 g/20 g; OLETH-3 PHOSPHATE 0.5 g/20 g; OLETH-10 PHOSPHATE 0.28 g/20 g; WATER 14.1 g/20 g; SODIUM HYDROXIDE 0.24 g/20 g; TEA TREE OIL 0.2 g/20 g; .ALPHA.-TOCOPHEROL ACETATE 0.1 g/20 g

After Bite Kids

Active Ingredient

Sodium Bicarbonate (Baking Soda) 5%

Purpose

Skin Protectant

Uses

Temporarily protects and helps relieve minor skin irritation and itching due to

- Insect bites
- Poison ivy, oak, or sumac

Warnings

for external use only..

When using this product

do not get into eyes

Stop use and ask a doctor if

- condition worsens
- symptoms last more than 7 days or clear up and occur again within a few days

Keep Out of Reach of Children.

If swallowed, get medical help or contact a Poison Control Center right away.
If in eyes flush with water for 15 minutes and call a doctor.

Directions

Use cap to puncture safety seal.

- Adults and children 2 years and older for use as a cream, apply to the affected area of the skin as needed or as directed by a doctor
- Children under 2 years ask a doctor

Inactive Ingredients

Aloe Vera, Dimethicone, Emulsifying Wax, Eucalyptus Oil, Oleth-3 Phosphate, Oleth-10 Phosphate, Purified Water, Sodium Hydroxide, Tea Tree Oil and Vitamin E Acetate